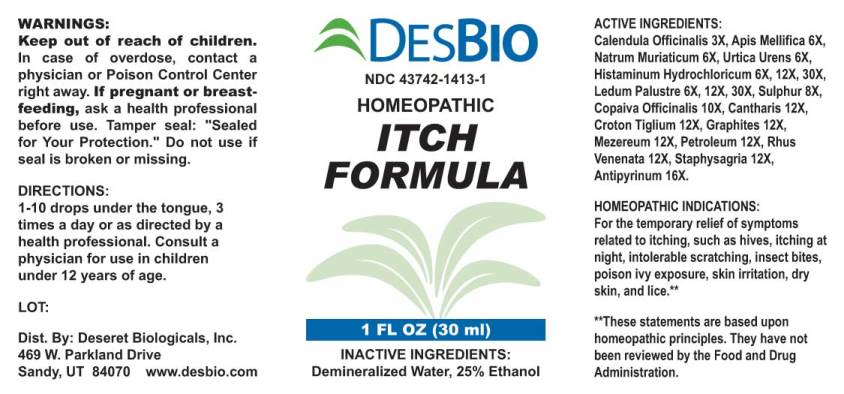 DRUG LABEL: Itch Formula
NDC: 43742-1413 | Form: LIQUID
Manufacturer: Deseret Biologicals, Inc.
Category: homeopathic | Type: HUMAN OTC DRUG LABEL
Date: 20240911

ACTIVE INGREDIENTS: CALENDULA OFFICINALIS FLOWERING TOP 3 [hp_X]/1 mL; APIS MELLIFERA 6 [hp_X]/1 mL; SODIUM CHLORIDE 6 [hp_X]/1 mL; HISTAMINE DIHYDROCHLORIDE 6 [hp_X]/1 mL; RHODODENDRON TOMENTOSUM LEAFY TWIG 6 [hp_X]/1 mL; SULFUR 6 [hp_X]/1 mL; COPAIFERA OFFICINALIS RESIN 8 [hp_X]/1 mL; LYTTA VESICATORIA 10 [hp_X]/1 mL; CROTON TIGLIUM SEED 12 [hp_X]/1 mL; GRAPHITE 12 [hp_X]/1 mL; DAPHNE MEZEREUM BARK 12 [hp_X]/1 mL; KEROSENE 12 [hp_X]/1 mL; TOXICODENDRON VERNIX LEAFY TWIG 12 [hp_X]/1 mL; DELPHINIUM STAPHISAGRIA SEED 12 [hp_X]/1 mL; ANTIPYRINE 16 [hp_X]/1 mL
INACTIVE INGREDIENTS: WATER; ALCOHOL

Drug Facts:

ACTIVE INGREDIENTS:

Calendula Officinalis 3X, Apis Mellifica 6X, Natrum Muriaticum 6X, Urtica Urens 6X, Histaminum Hydrochloricum 6X, 12X, 30X, Ledum Palustre 6X, 12X, 30X, Sulphur 8X, Copaiva Officinalis 10X, Cantharis 12X, Croton Tiglium 12X, Graphites 12X, Mezereum 12X, Petroleum 12X, Rhus Venenata 12X, Staphysagria 12X, Antipyrinum 16X.

HOMEOPATHIC INDICATIONS:

For the temporary relief of symptoms related to itching, such as hives, itching at night, intolerable scratching, insect bites, poison ivy exposure, skin irritation, dry skin, and lice.**

**These statements are based upon traditional homeopathic principles. They have not been reviewed by the Food and Drug Administration.

WARNINGS:

Keep out of reach of children. In case of overdose, contact a physician or Poison Control Center right away.

If pregnant or breast-feeding, ask a health professional before use.

Tamper seal: "Sealed for Your Protection."

Do not use if seal is broken or missing.

Keep out of reach of children. In case of overdose, contact a physician or Poison Control Center right away.

DIRECTIONS:

1-10 drops under the tongue, 3 times a day or as directed by a health professional. Consult a physician for use in children under 12 years of age.

HOMEOPATHIC INDICATIONS:

For the temporary relief of symptoms related to itching, such as hives, itching at night, intolerable scratching, insect bites, poison ivy exposure, skin irritation, dry skin, and lice.**

**These statements are based upon traditional homeopathic principles. They have not been reviewed by the Food and Drug Administration.

INACTIVE INGREDIENTS:

Demineralized Water, 25% Ethanol

QUESTIONS:

Dist. By: Deseret Biologicals, Inc.

469 W. Parkland Drive

Sandy, UT 84070 www.desbio.com

PACKAGE LABEL DISPLAY:

DESBIO

NDC 43742-1413-1

HOMEOPATHIC

ITCH

FORMULA

1 FL OZ (30 ml)